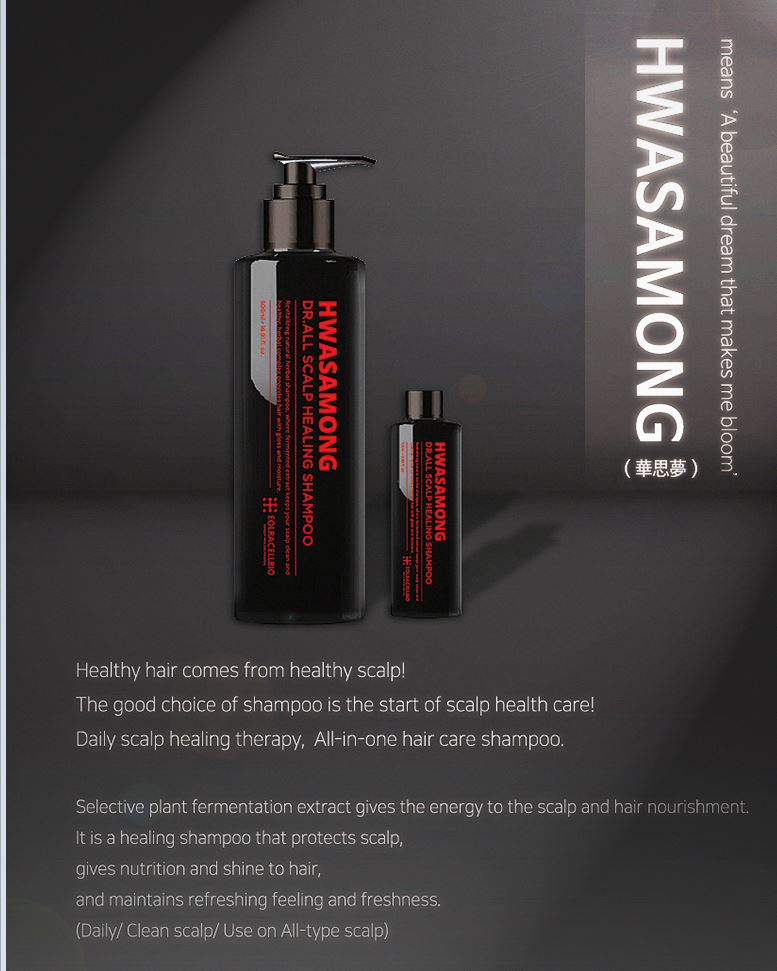 DRUG LABEL: HWASAMONG Dr.All Scalp HealingShampoo
NDC: 76678-0001 | Form: SHAMPOO
Manufacturer: Eolracellbio Co., Ltd.
Category: otc | Type: HUMAN OTC DRUG LABEL
Date: 20200502

ACTIVE INGREDIENTS: BETAINE 0.5 g/100 mL; PANTHENOL 0.3 g/100 mL
INACTIVE INGREDIENTS: NIACINAMIDE; WATER; GLYCERIN

Drug Facts

ACTIVE INGREDIENT

biotin, panthenol

PURPOSE

hair care, ph balanced shampoo

KEEP OUT OF REACH OF THE CHILDREN

WARNINGS

■ For external use only.

■ Do not use in eyes.

■ lf swallowed, get medical help promptly.

■ Stop use, ask doctor lf irritation occurs.

■ Keep out of reach of children.

DOSAGE AND ADMINISTRATION

for external use only

INACTIVE INGREDIENT

Water
Disodium Cocoamphodiacetate
Sodium Cocoyl Isethionate
Potassium Cocoyl Glycinate
Lauryl Glucoside
Decyl Glucoside
Glycerin
LoniceraJaponica(Honeysuckle)FlowerExtract
EcliptaProstrataExtract
CitrusUnshiuPeelExtract
MenthaArvensisExtract
PolygonumMultiflorumRootExtract
BiotaOrientalisLeafExtract
MorusAlbaLeafExtract
HouttuyniaCordataExtract
GlycineSoja(Soybean)SeedExtract
EckloniaCavaExtract
PerillaFrutescensLeafExtract
Acrylates/C10-30 Alkyl Acrylate Crosspolymer
Arginine
Polyquaternium-10
Allantoin
Niacinamide
Butylene Glycol
1,2-Hexanediol
Caprylyl Glycol
Illicium Verum (Anise) Fruit Extract
Citric Acid
Disodium EDTA
Sodium Hyaluronate
Zinc Pyrithione
Menthol
Fragrance

INDICATIONS AND USAGE

combine hair before shampoo to remove large dust

gently massage shampoo into wet hair and scalp all over your tips

rinse to remove any remaining dubbles

tap wet hair with a toweland let it dry in natural or cold wind